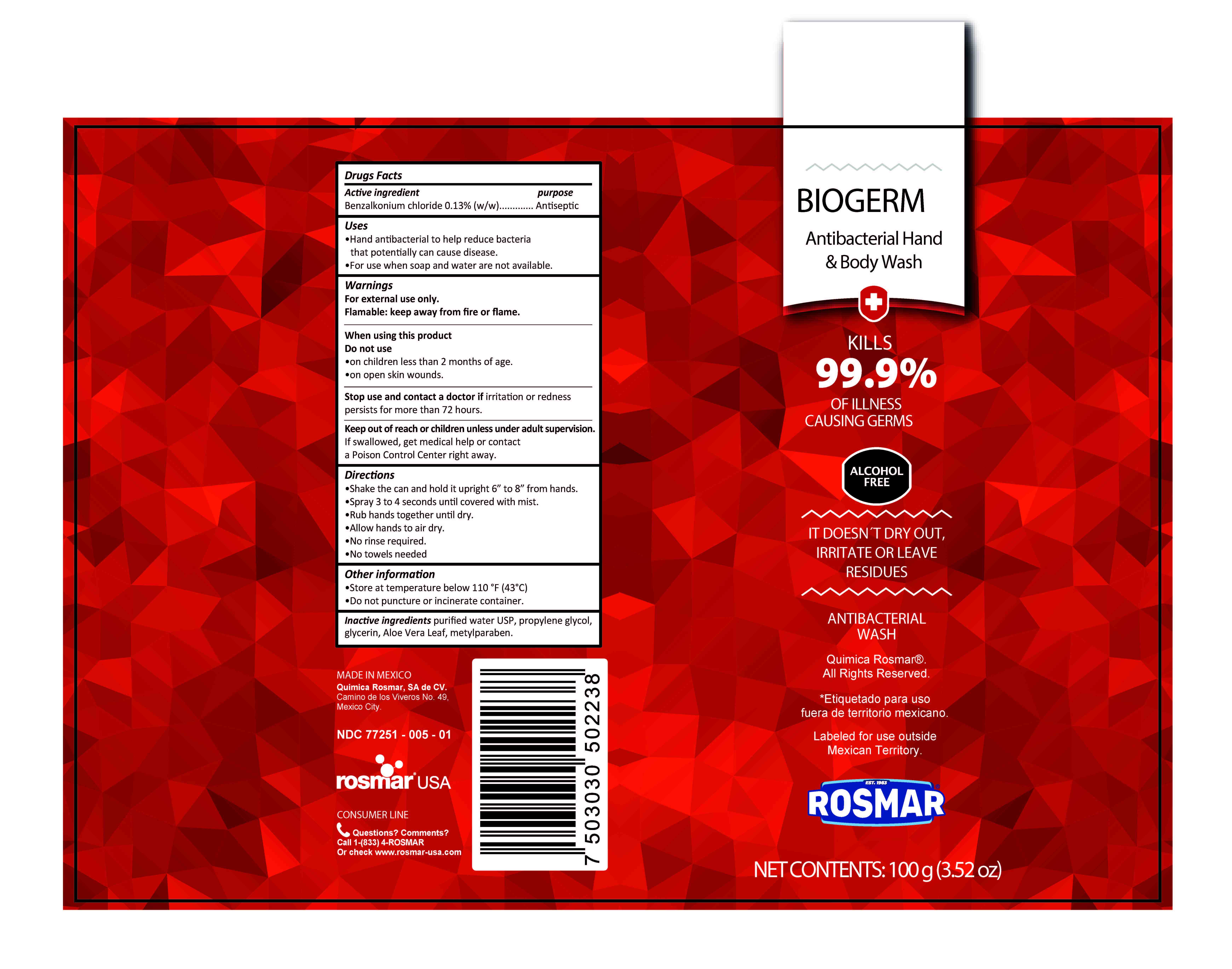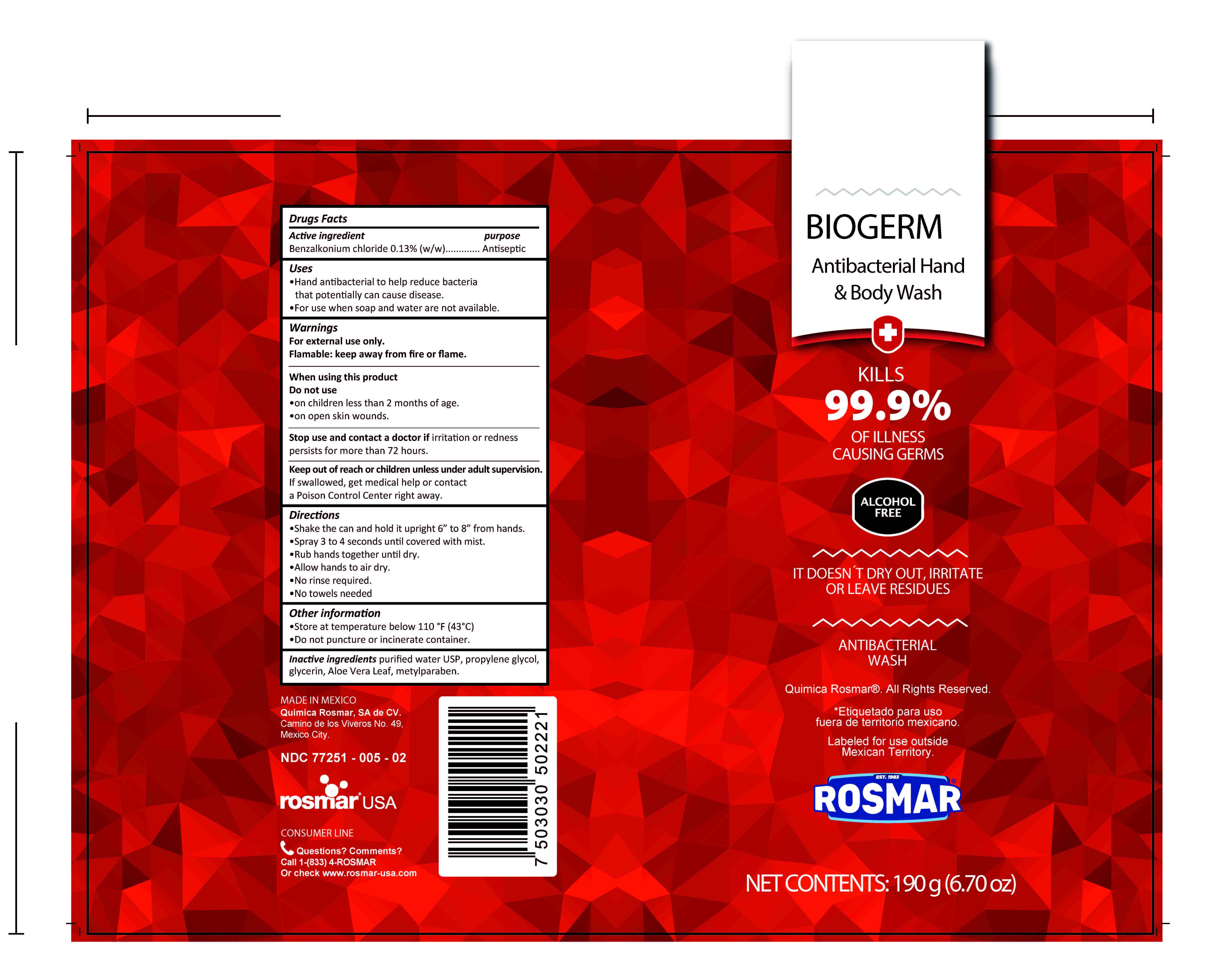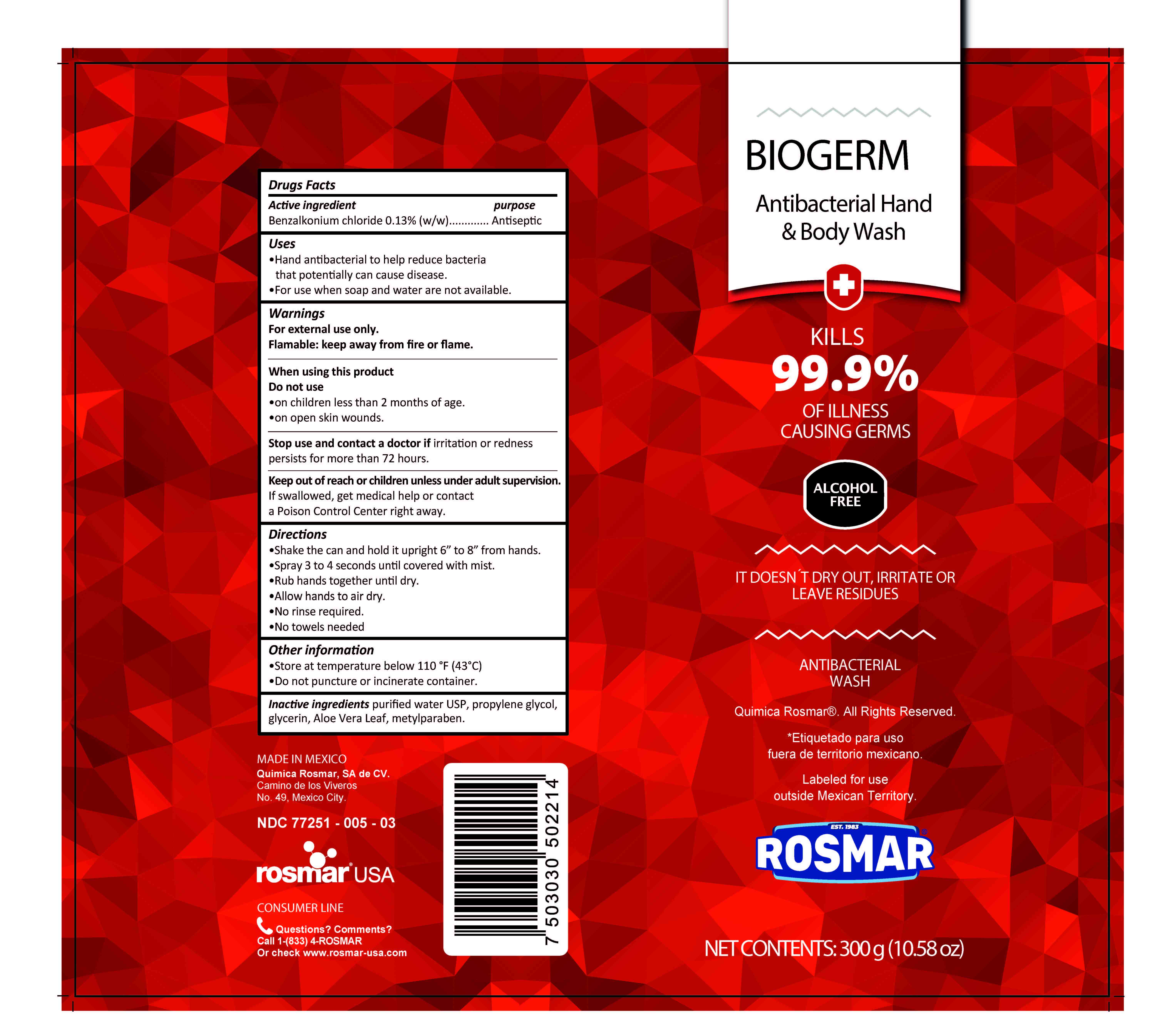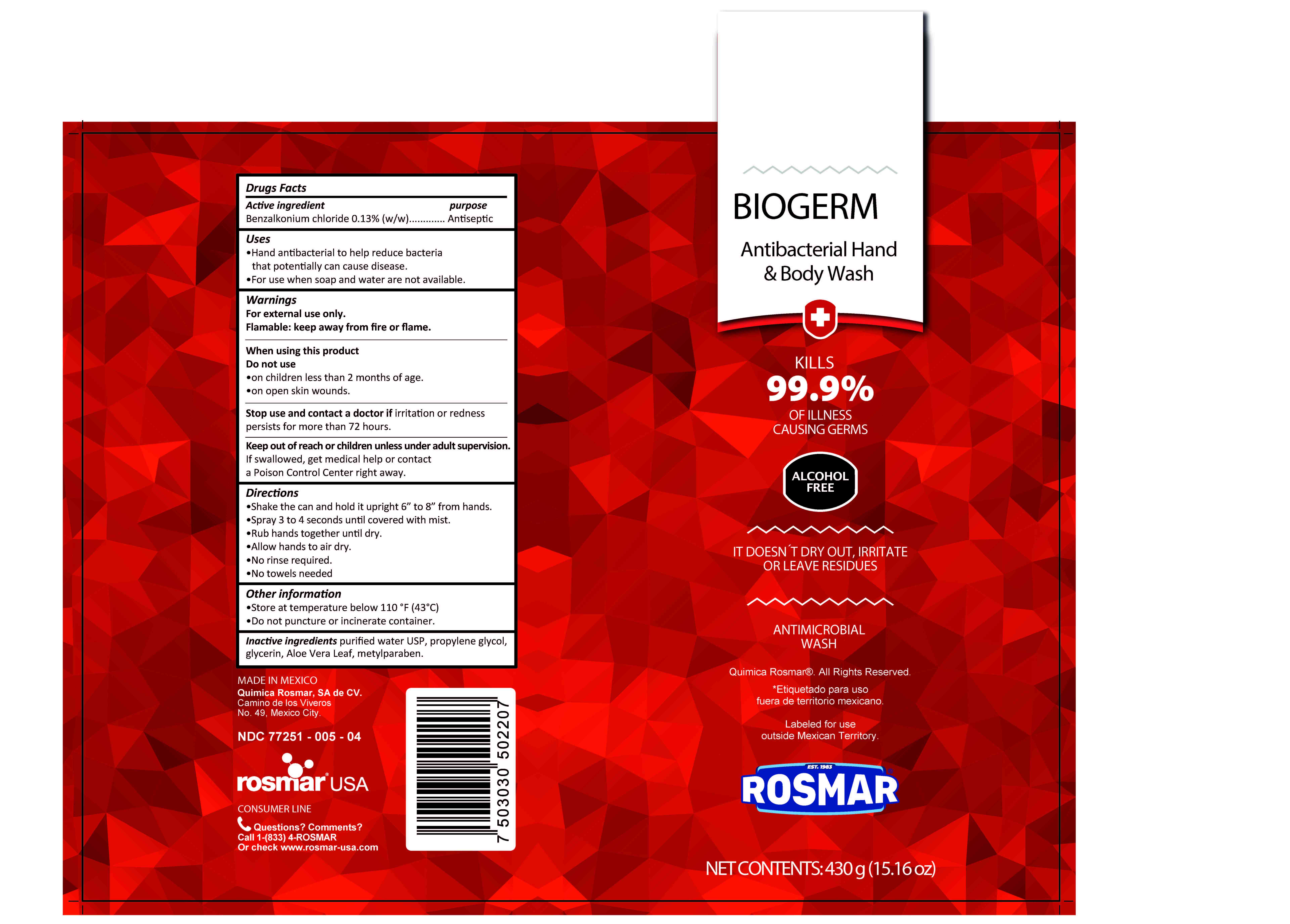 DRUG LABEL: BioGerm Sanitizer
NDC: 77251-005 | Form: SPRAY
Manufacturer: QUIMICA ROSMAR S.A. DE C.V.
Category: otc | Type: HUMAN OTC DRUG LABEL
Date: 20211018

ACTIVE INGREDIENTS: BENZALKONIUM CHLORIDE 0.13 g/100 g
INACTIVE INGREDIENTS: GLYCERIN; PROPYLENE GLYCOL; WATER; ALOE VERA LEAF; METHYLPARABEN

77251-005 Benzalkonium chloride 0.13%

Active Ingredient(s)

Benzalkonium Chloride 0.13% v/v. Purpose: Antiseptic

Purpose

Antiseptic, full body Sanitizer

Use

Full body Sanitizer to help reduce bacteria that potentially can cause disease. For use when soap and water are not available.

Warnings

For external use only. Flammable. Keep away from heat or flame

Do not use

- in children less than 2 months of age
- on open skin wounds

When using this product keep out of eyes, ears, and mouth. In case of contact with eyes, rinse eyes thoroughly with water.
Stop use and ask a doctor if irritation or rash occurs. These may be signs of a serious condition.
Keep out of reach of children. If swallowed, get medical help or contact a Poison Control Center right away.

Stop use and ask a doctor if irritation or rash occurs. These may be signs of a serious condition.

Keep out of reach of children. If swallowed, get medical help or contact a Poison Control Center right away.

Directions

- Place enough product on hands to cover all surfaces. Rub hands together until dry.
- Supervise children under 6 years of age when using this product to avoid swallowing.

Other information

- Store between 15-30C (59-86F)
- Avoid freezing and excessive heat above 40C (104F)

Inactive ingredients

Propylene glycol, glycerin, aloe vera leaf, water, metylparaben

Package Label - Principal Display Panel

60 g NDC: 77251-005-01

190 g NDC: 77251-005-02

300 g NDC: 77251-005-03

430 g NDC: 77251-005-04